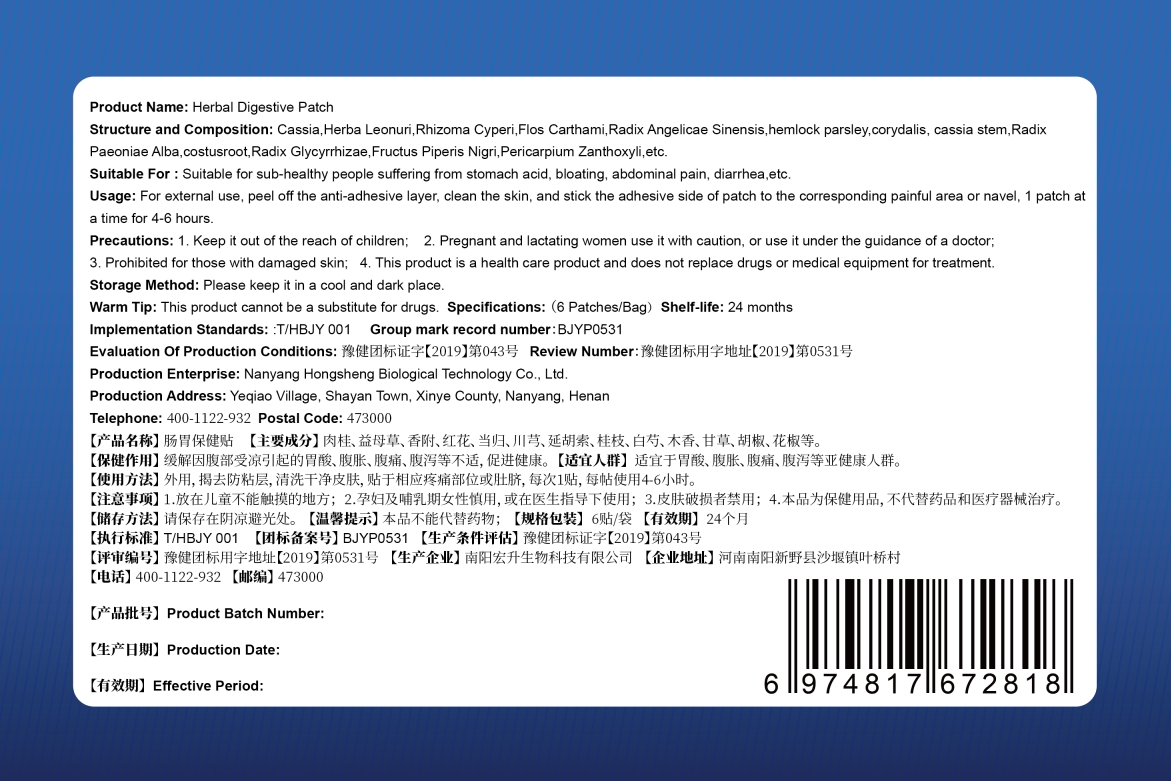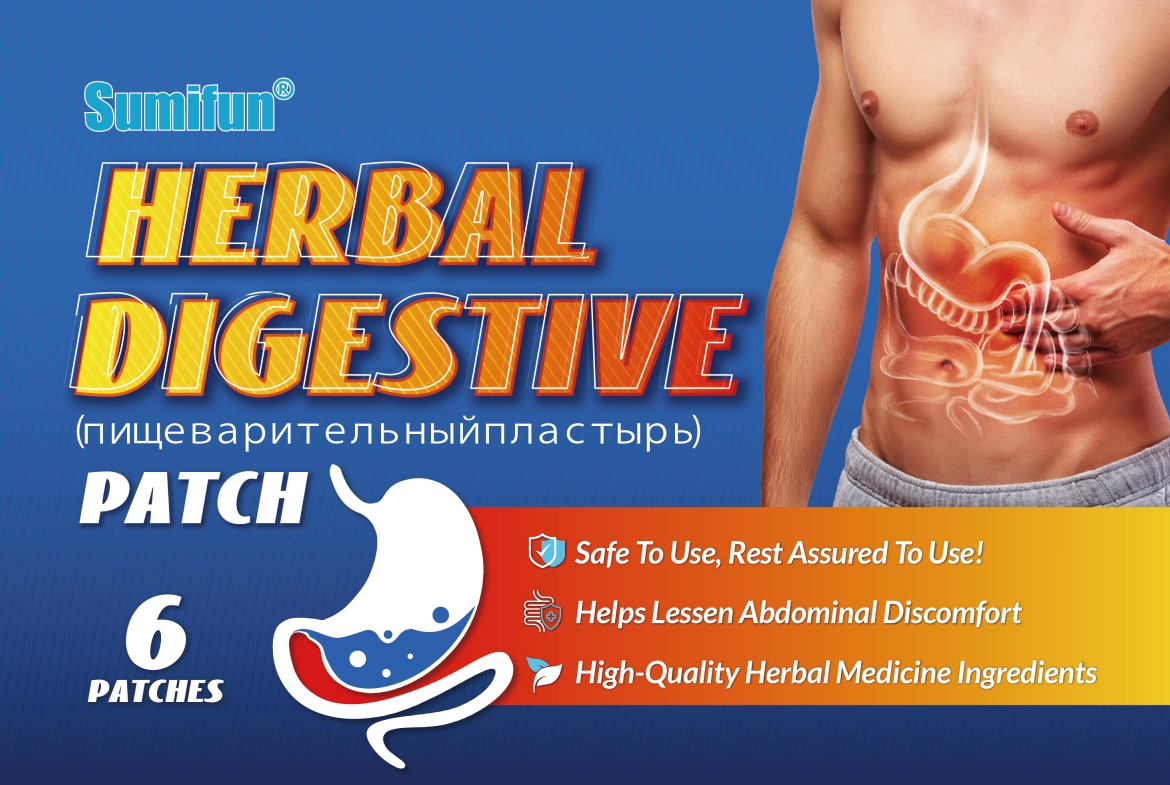 DRUG LABEL: Herbal Digestive Patch
NDC: 83675-004 | Form: PATCH
Manufacturer: Guangzhou Hanhai Trading Co., Ltd
Category: otc | Type: HUMAN OTC DRUG LABEL
Date: 20230919

ACTIVE INGREDIENTS: PADANG CASSIA 16 g/100 1
INACTIVE INGREDIENTS: SENNA OBTUSIFOLIA SEED; PAEONIA LACTIFLORA ROOT; RUBUS CHINGII WHOLE; CYPERUS ROTUNDUS ROOT; SAFFLOWER; COSTUS SPICATUS ROOT; GLYCYRRHIZA INFLATA ROOT; ZANTHOXYLUM BUNGEANUM WHOLE; LEONURUS JAPONICUS FLOWERING TOP; ANGELICA SINENSIS ROOT; PARSLEY; DICENTRA CANADENSIS ROOT

83675-004-01
Herbal Digestive Patch

Active Ingredient

Cassia 16.0%

Purpose

Help Lessen Abdominal Discomfort

Use

Herbal Digestive Patch to help lessen abdominal discomfort

Warnings

For external use only. Do not take it internally.

Keep Out Of Reach Of Children
Pregnant and lactating women use it with caution

Do not use

Product shall not be eat

When Using

Do not stick around eyes and mouth,This product cannot replace drugs or medical equipment for treatment

Stop Use

In case of adverse reactions, please stop using this product.If the symptoms.

Ask Doctor

ask doctor in case of adverse reactions

Keep Oot Of Reach Of Children

Keep Out Of Reach Of Children

Directions

Take one piece of this product when needed, remove the waxpaper, stick to the

desired area and press the surrounding, replace it every 4-6 hours.

Children should be used under adult supervision.

Other information

Store the product in a cool, dry and well-ventilated place

Avoid direct sunlight

Inactive ingredients

Herba Leonur,

Rhizoma Cyperi,

Flos Carthami,

Radx Angelicae Sinensis,

hemlock parsley,

corydalis,

cassia stem.

RadixPaeoniae Alba,

costusroot,

Radix Glycyrrhizae,

Fructus Piperis Nigri,

Pericarpium Zanthoxyli